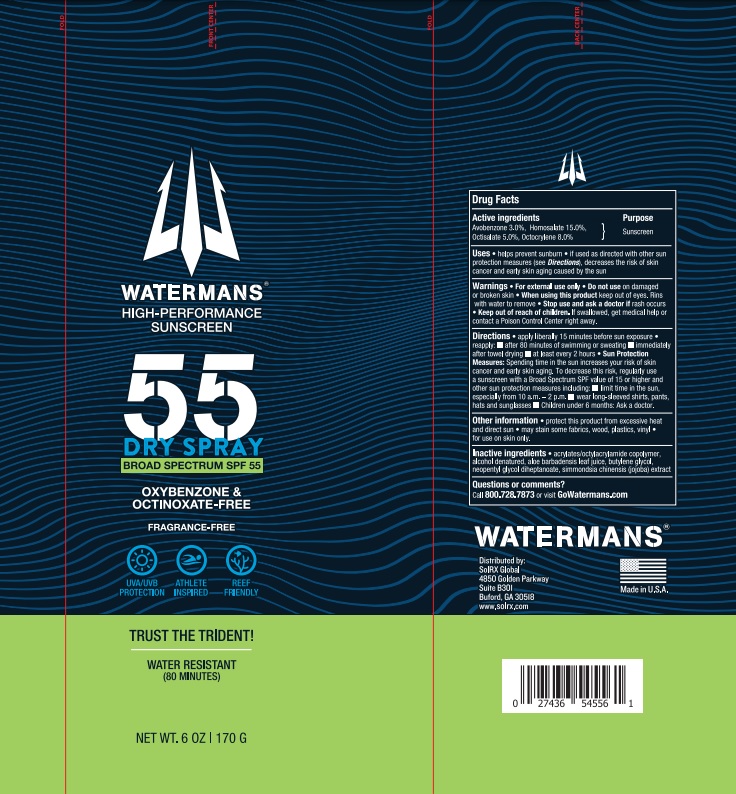 DRUG LABEL: Watermans SPF 55
NDC: 73440-6000 | Form: SPRAY
Manufacturer: Cross Brands Contract Filling
Category: otc | Type: HUMAN OTC DRUG LABEL
Date: 20210802

ACTIVE INGREDIENTS: HOMOSALATE 25.5 g/170 g; AVOBENZONE 5.1 g/170 g; OCTISALATE 8.5 g/170 g; OCTOCRYLENE 13.6 g/170 g
INACTIVE INGREDIENTS: ALCOHOL 106.93 g/170 g

Watermans High-Performance Sunscreen Dry Spray Broad Spectrum SPF 55